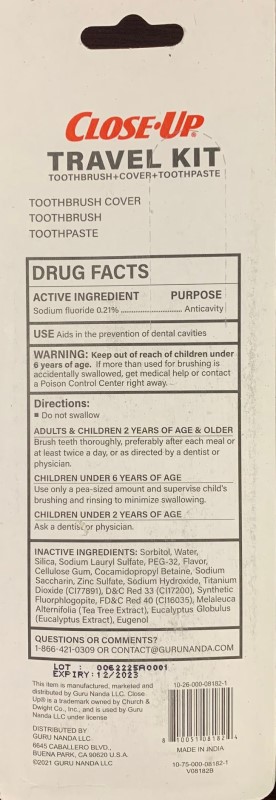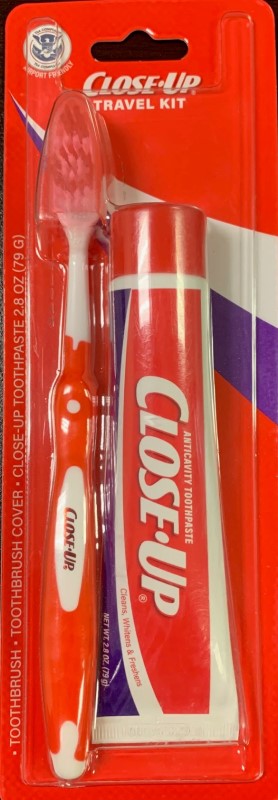 DRUG LABEL: CLOSEUP TRAVEL
NDC: 70708-182 | Form: PASTE, DENTIFRICE
Manufacturer: GURUNANDA, LLC
Category: otc | Type: HUMAN OTC DRUG LABEL
Date: 20220810

ACTIVE INGREDIENTS: SODIUM FLUORIDE 0.21 g/100 g
INACTIVE INGREDIENTS: EUCALYPTUS GLOBULUS WHOLE; SACCHARIN SODIUM; D&C RED NO. 33; COCAMIDOPROPYL BETAINE; WATER; SORBITOL; TITANIUM DIOXIDE; FD&C RED NO. 40; EUGENOL; MELALEUCA ALTERNIFOLIA WHOLE; SODIUM SILICATE; ZINC SULFATE; SODIUM HYDROXIDE; ALPHA CELLULOSE; SODIUM LAURYL SULFATE; PEG-32 LAURATE

CLOSEUP TOOTHPASTE 79 GM

ACTIVE INGREDIENTS

Sodium Fluoride 0.21%

PURPOSE

Anticavity

USE

Aids in the prevention of dental cavities

WARNING

If more than used for brushing is accidentally swallowed, get medical help or contact a Poison Control Center right away.

Keep out of reach of children under 6 years of age.

DIRECTIONS

Do not swallow.

- Adults and children 2 years and older: Brush teeth thoroughly, preferably after each meal or at least twice a day, or as directed by a dentist or physician.

- Children under 6 Years of Age: Use only a pea-sized amount and supervise children's brushing and rinsing to minimize swallowing.

- Children under 2 years of age: Ask a dentist or physician

INACTIVE INGREDIENTS

Sorbitor, Water, Silica, Sodium Lauryl Suphate, PEG-32, Titanium Dioxide, Flavor, Cellulose Gum, Cocamidopropyl Betaine, Sodium Saccharin, Zinc Sulfate, Sodium Hydroxide, D&C Red 33, FD&C Red 40, Synthetic Fluorphlogopite, Melaleuca Alternifolia (Tea Tree Extract), Eucalyptus Globulus (Eucalyptus Extract), Eugenol

QUESTIONS

1-866-421-0309